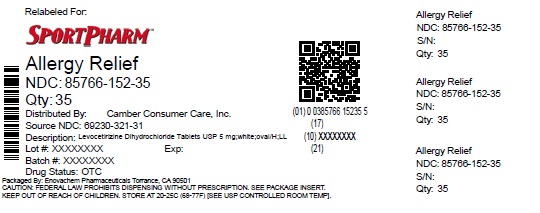 DRUG LABEL: Levocetirizine Dihydrochloride
NDC: 85766-152 | Form: TABLET, FILM COATED
Manufacturer: Sportpharm LLC
Category: otc | Type: HUMAN OTC DRUG LABEL
Date: 20260214

ACTIVE INGREDIENTS: LEVOCETIRIZINE DIHYDROCHLORIDE 5 mg/1 1
INACTIVE INGREDIENTS: LACTOSE MONOHYDRATE; MICROCRYSTALLINE CELLULOSE; SILICON DIOXIDE; MAGNESIUM STEARATE; TITANIUM DIOXIDE; HYPROMELLOSE 2910 (3 MPA.S); HYPROMELLOSE 2910 (6 MPA.S); POLYETHYLENE GLYCOL 400; POLYSORBATE 80

Levocetirizine Dihydrochloride Tablets USP, 5 mg (OTC)

ACTIVE INGREDIENT(S)

Levocetirizine dihydrochloride USP 5 mg

PURPOSE

Antihistamine

USE(S)

temporarily relieves these symptoms due to hay fever or other respiratory allergies:
• runny nose
• sneezing
• itchy, watery eyes
• itching of the nose or throat

DO NOT USE

• if you have kidney disease
• if you have ever had an allergic reaction to this product or any of its ingredients or to an antihistamine containing cetirizine

ASK A DOCTOR BEFORE USE IF YOU HAVE

- ever had trouble urinating or emptying your bladder

WHEN USING THIS PRODUCT

- drowsiness may occur
- avoid alcoholic drinks
- alcohol, sedatives, and tranquilizers may increase drowsiness
- be careful when driving a motor vehicle or operating machinery

STOP USE AND ASK A DOCTOR IF

• you have trouble urinating or emptying your bladder
• an allergic reaction to this product occurs. Seek medical help right away.

IF PREGNANT OR BREAST-FEEDING

- if breast-feeding: not recommended
- if pregnant: ask a health professional before use

KEEP OUT OF REACH OF CHILDREN

In case of overdose, get medical help or contact a Poison Control Center right away (1-800-222-1222).

DIRECTIONS

adults 65 years of age and older | - ask a doctor
adults and children 12 to 64 years of age | - take 1 tablet (5 mg) once daily in the evening - do not take more than 1 tablet (5 mg) in 24 hours - ½ tablet (2.5 mg) once daily in the evening may be appropriate for less severe symptoms
children 6 to 11 years of age | - take ½ tablet (2.5 mg) once daily in the evening - do not take more than ½ tablet (2.5 mg) in 24 hours
children under 6 years of age | - do not use
consumers with kidney disease | - do not use

OTHER INFORMATION

• store between 20° and 25°C (68° and 77°F)
• safety sealed: do not use if carton was opened or if printed foil inner seal on bottle is torn or missing
• safety sealed: do not use if carton was opened or if individual blister unit is open or torn

INACTIVE INGREDIENTS

colloidal silicon dioxide, hypromellose, lactose monohydrate, magnesium stearate, microcrystalline cellulose, polyethylene glycol, polysorbate 80, titanium dioxide.

QUESTIONS or COMMENTS?

call 1-888-588-1418.

Distributed by:

Sportpharm LLC

379 Van Ness Ave 1401,

Torrance, CA 90501

Relabeled by:

Enovachem PHARMACEUTICALS

Torrance, CA 90501